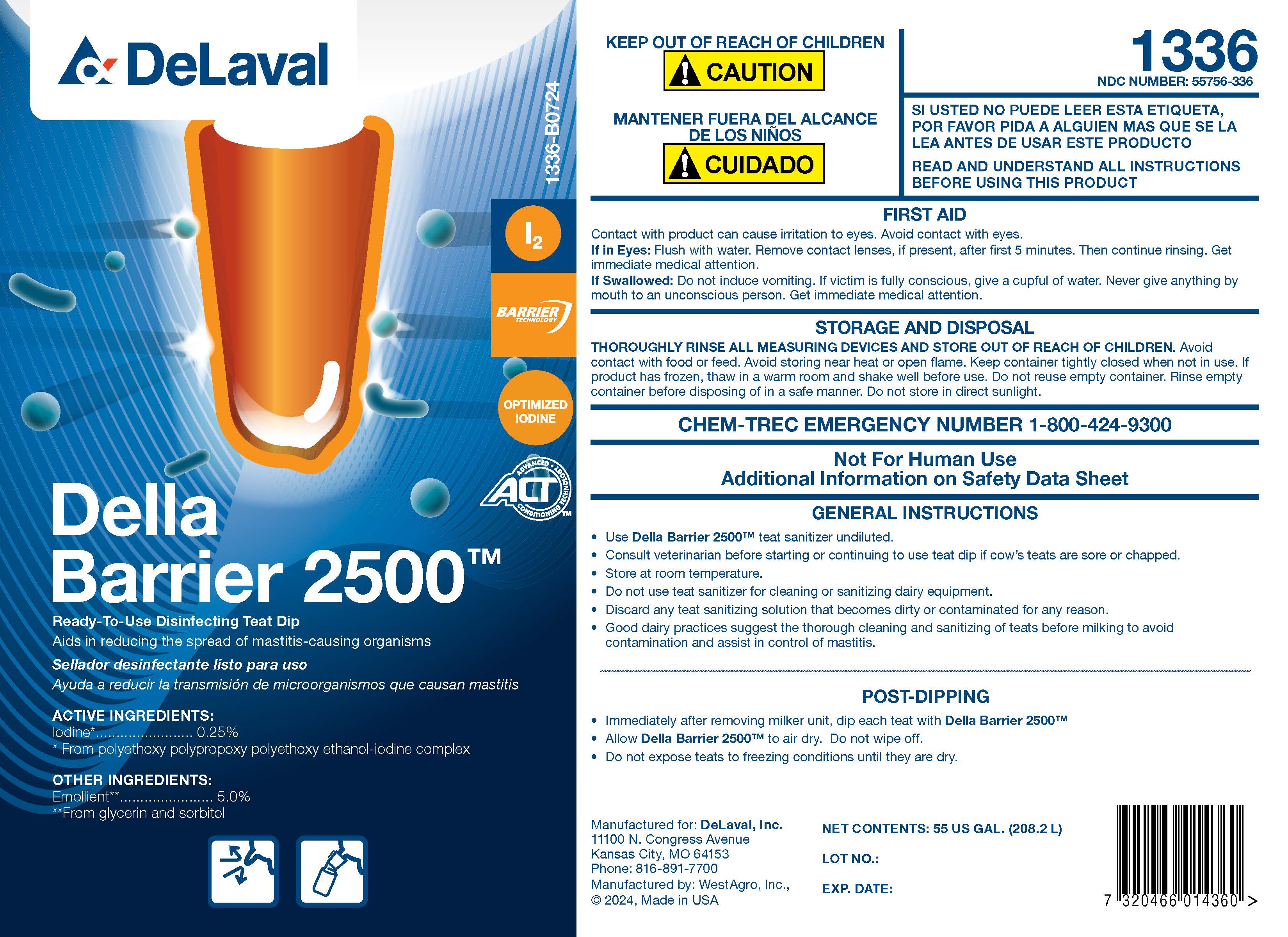 DRUG LABEL: Della Barrier 2500
NDC: 55756-336 | Form: SOLUTION
Manufacturer: DeLaval
Category: animal | Type: OTC ANIMAL DRUG LABEL
Date: 20240924

ACTIVE INGREDIENTS: IODINE .0025 g/1 L
INACTIVE INGREDIENTS: GLYCERIN; SODIUM HYDROXIDE; ANHYDROUS CITRIC ACID; XANTHAN GUM; POVIDONE K30; POLOXAMER 335; SORBITOL SOLUTION 70%; SODIUM CHLORIDE; SODIUM IODATE; WATER

Della Barrier 2500TM

ACTIVE INGREDIENTS:

Iodine*.......................0.25%

*From polyethoxy polypropoxy polyethoxy ethanol-iodine complex

Emollient**.................5.0%

**From glycerine and sorbitol

PURPOSE

Ready-To-Use Disinfecting Teat Dip

Aids in reducing the spread of mastitis-causing organisms

KEEP OUT OF REACH OF CHILDREN

! CAUTION

MANTENER FUERA DEL ALCANCE DE LOS NIÑOS

! CUIDADO

SI USTED NO PUEDE LEER ESTA ETIQUETA, POR FAVOR PIDA A ALGUIEN MAS QUE SE LA LEA ANTES DE USAR ESTE PRODUCTO

READ AND UNDERSTAND ALL INSTRUCTIONS BEFORE USING THIS PRODUCT

FIRST AID

Contact with product can cause irritation to eyes. Avoid contact with eyes.

If in Eyes: Flush with water. Remove contact lenses, if present, after first 5 minutes. Then continue rinsing. Get immedicate medical attention.

If Swallowed: Do not induce vomiting. If victim is fully conscious, give a cupful of water. Never give anything by mouth to an unconscious person. Get immediate medical attention.

STORAGE AND DISPOSAL

THOROUGHLY RINSE ALL MEASURING DEVICES AND STORE OUT OF REACH OF CHILDREN. Avoid contact with food or feed. Avoid storing near heat or open flame. Keep container tightly closed when not in use. If product has frozen, thaw in a warm room and shake well before use. Do not reuse empty container. Rinse empty container before disposing of in a safe manner. Do not store in direct sunlight.

CHEM-TREC EMERGENCY NUMBER 1-800-424-9300

WARNINGS

Not For Human Use

Additional Information on Safety Data Sheet

INDICATIONS AND USAGE

GENERAL INSTRUCTIONS

- Use Della Barrier 2500TM teat sanitizer undiluted.
- Consult veterinarian before starting or continuing to use teat dip if cow's teats are sore or chapped.
- Store at room temperature.
- Do not use teat sanitizer for cleaning or sanitizing dairy equipment.
- Discard any teat sanitizing solution that becomes dirty or contaminated for any reason.
- Good dairy practices suggest the thorough cleaning and sanitizing of teats before milking to avoid contamination and assist in control of mastitis.

POST-DIPPING

- Immediately after removing milker unit, dip each teat with Della Barrier 2500TM
- Allow Della Barrier 2500TM to air dry. Do not wipe off.
- Do not expose teats to freezing conditions until they are dry.

Manufactured for: DeLaval, Inc.

11100 N. Congress Avenue

Kansas City, MO 64153

Phone: 816-891-7700

Manufactured by: WestAgro, Inc.

©2024. Made in USA

NET CONTENTS:

LOT NO.:

EXP. DATE:

PACKAGE LABEL

Add image transcription here...